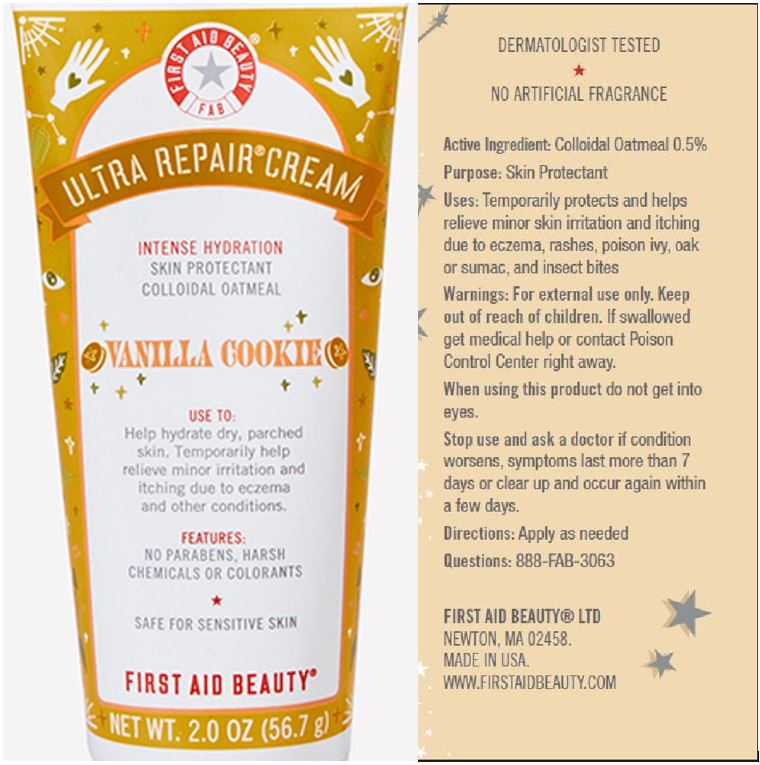 DRUG LABEL: First Aid Beauty FAB Ultra Repair Skin Protectant Vanilla Cookie
NDC: 69423-708 | Form: CREAM
Manufacturer: The Procter & Gamble Manufacturing Company
Category: otc | Type: HUMAN OTC DRUG LABEL
Date: 20251218

ACTIVE INGREDIENTS: OATMEAL 0.5 g/100 g
INACTIVE INGREDIENTS: CETOSTEARYL ALCOHOL; SQUALANE; DIMETHICONE; TANACETUM PARTHENIUM WHOLE; EDETATE DISODIUM; GLYCERYL STEARATE SE; ALKYL (C12-15) BENZOATE; GREEN TEA LEAF; CAPRYLYL GLYCOL; SODIUM HYDROXIDE; PHENOXYETHANOL; SHEA BUTTER; GLYCYRRHIZA GLABRA; WATER; GLYCERIN; ALLANTOIN; GLYCERYL MONOSTEARATE; MEDIUM-CHAIN TRIGLYCERIDES; STEARIC ACID; XANTHAN GUM; LAVANDULA ANGUSTIFOLIA FLOWER; CERAMIDE NP; BALSAM PERU OIL; VANILLIN

First Aid Beauty FAB Ultra Repair Cream Skin Protectant Vanilla Cookie

Drug Facts

Active ingredients

Colloidal Oatmeal 0.5%

Purpose

Skin Protectant

Uses

- Temporarily protects and helps relieve minor skin irritation and itching due to eczema, rashes, poison ivy, oak or sumac, insect bites

Warnings

For external use only.

Keep out of reach of children. If swallowed, get medical help or contact a Poison Control Center right away.

WHEN USING

Do not get into eyes.

Stop use and ask a doctor if condition worsens, symptoms last more than 7 days or clear up and occur again within a few days

Directions

Apply as needed

INACTIVE INGREDIENT

Water, stearic acid, glycerin, c12-15 alkyl benzoate, caprylic/capric triglyceride, glyceryl stearate, glyceryl stearate se, cetearyl alcohol, dimethicone, squalane, butyrospermum parkii (shea) butter, phenoxyethanol, caprylyl glycol, xanthan gum, allantoin, sodium hydroxide, disodium edta, chrysanthemum parthenium (feverfew) extract, camellia sinensis leaf extract, glycyrrhiza glabra (licorice) root extract, ceramide-3, lavandula angustifolia (lavender), myroxylon pereira (peru balsam) oil, vanillin

Questions:

888-FAB-3063

MADE IN USA

FIRST AID BEAUTY LTD

NEWTON, MA 02458

WWW.FIRSTAIDBEAUTY.COM

PRINCIPAL DISPLAY PANEL - 2.0 oz (56.7 g)

First Aid Beauty

FAB

Ultra Repair® Cream

Intense Hydration

Skin Protectant

Colloidal Oatmeal

VANILLA COOKIE

FIrst Aid Beauty ®

Net Wt. 2.0 oz (56.7 g)